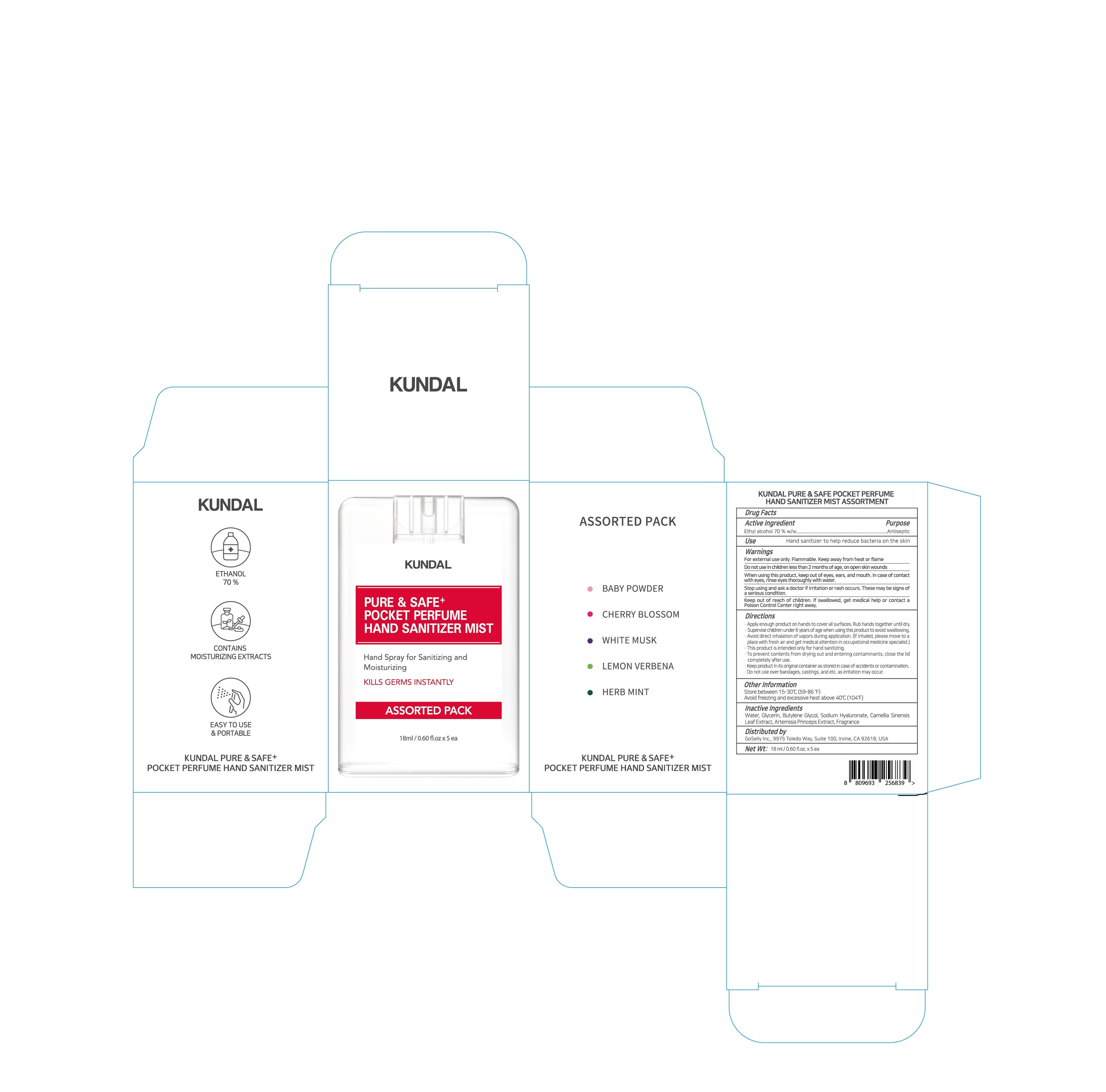 DRUG LABEL: KUNDAL PURE and SAFE SANITIZING WIPE (ETHANOL)
NDC: 74773-0029 | Form: LIQUID
Manufacturer: THESKINFACTORY Co., Ltd.
Category: otc | Type: HUMAN OTC DRUG LABEL
Date: 20201004

ACTIVE INGREDIENTS: ALCOHOL 50.967 g/100 g
INACTIVE INGREDIENTS: GREEN TEA LEAF; WATER; GLYCERIN; CALENDULA OFFICINALIS FLOWER

ACTIVE INGREDIENT

alcohol

INACTIVE INGREDIENT

Water
Glycerin
Camellia Sinensis Leaf Extract

calendula officinalis flower extract

PURPOSE

hand sanitizing tissue to help reduce bacteria on the skin

keep out of reach of the children

INDICATIONS AND USAGE

plae enough product on hands to cover all surfaces, rub hands together until dry

WARNINGS

For external use only. Flammable. Keep away from heat or flame.

Do not use

- in children less than 2 months of age
- on open skin wounds

When using this product keep out of eyes, ears, and mouth. In case of contact with eyes, rinse thoroughly with water.

Stop use and ask a doctor if irritation or rash occurs. These may be signs of a serious condition.

Keep out of reach of children. If swallowed, get medical help or contact a Poison Control Center right away.

DOSAGE AND ADMINISTRATION

for external use only